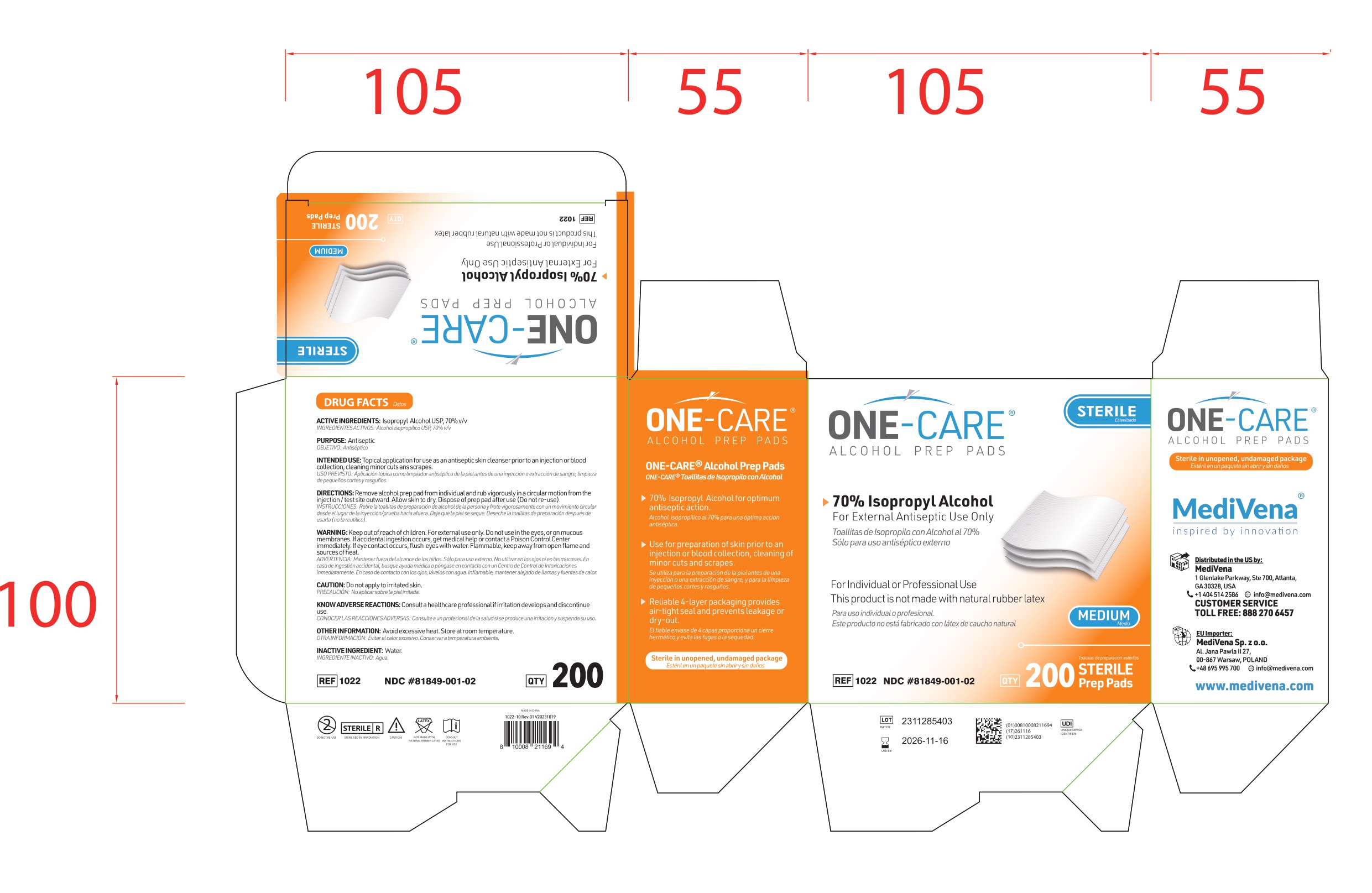 DRUG LABEL: Alcohol Pads
NDC: 81849-001 | Form: SOLUTION
Manufacturer: Shandong Lianfa Medical Plastic Products CO.,LTD
Category: otc | Type: HUMAN OTC DRUG LABEL
Date: 20231201

ACTIVE INGREDIENTS: ISOPROPYL ALCOHOL 70 mL/100 mL
INACTIVE INGREDIENTS: WATER

81849-001 Alcohol Prep Pad

Active Ingredient(s)

Isopropyl Alcohol 70% v/v

Purpose

Antiseptic

Use

Use for the preparation of skin prior to injection and to decrease germs in minor cuts and scrapes

Warnings

For external use only.

Flammable. Keep away from flame or fire

Stop use and ask a doctor if irritation develops

Keep out of reach of children except with adult supervision. If swallowed, get medical help or contact a Poison Control Center at 1-800-222-1222

Directions for use

Apply topically as needed to cleanse intended area. Discard after single use.

Other information

Shelf life: 36 months

Store below 104F (40C)

The product batch number and expiry date are shown on the packaging

Inactive ingredients

Water, Non-woven